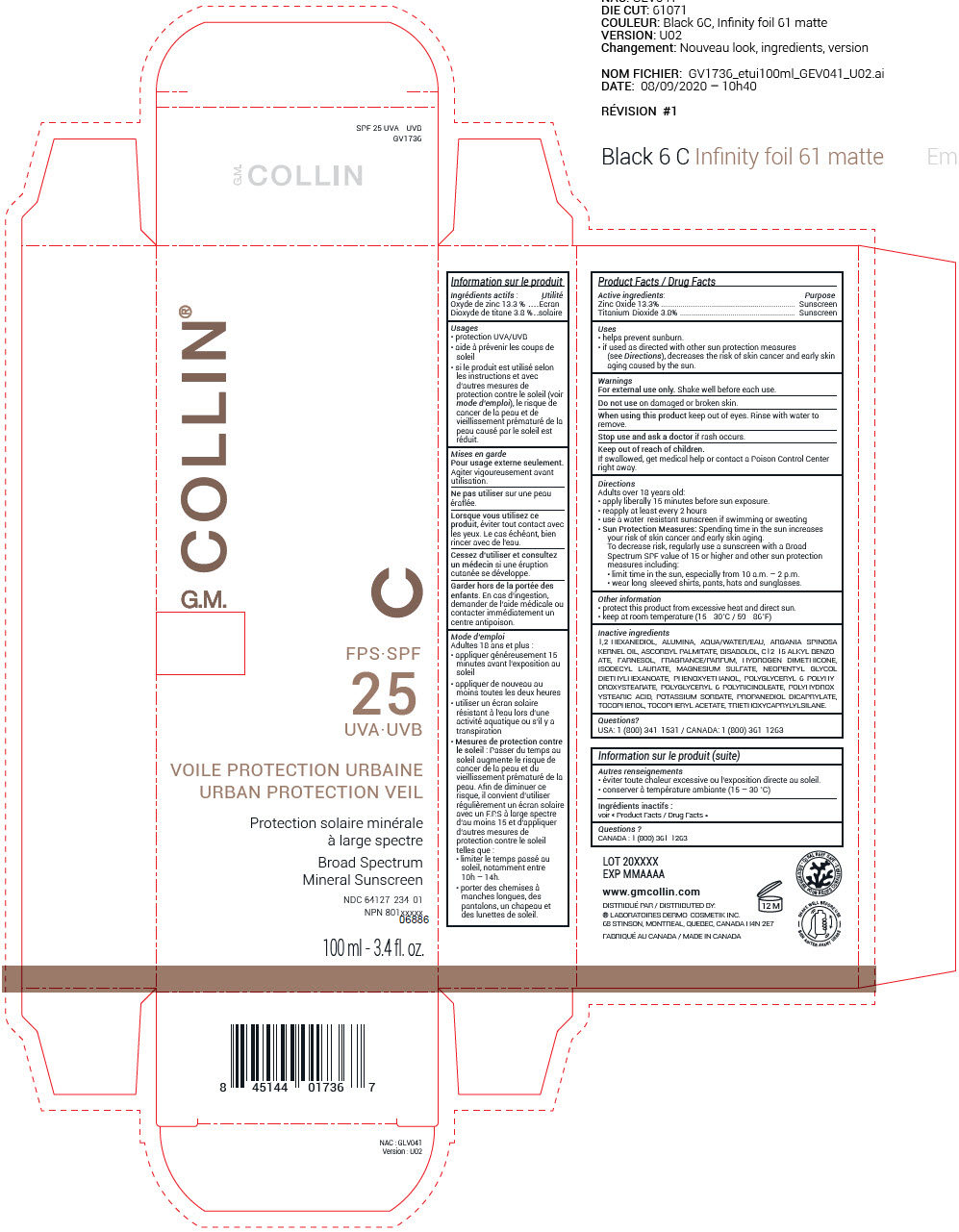 DRUG LABEL: GM Collin
NDC: 64127-234 | Form: CREAM
Manufacturer: Laboratoires Dermo-Cosmetik Inc.
Category: otc | Type: HUMAN OTC DRUG LABEL
Date: 20251218

ACTIVE INGREDIENTS: ZINC OXIDE 14.6 mg/100 mL; TITANIUM DIOXIDE 4.2 mg/100 mL
INACTIVE INGREDIENTS: 1,2-HEXANEDIOL; ALUMINUM OXIDE; WATER; ARGAN OIL; ASCORBYL PALMITATE; LEVOMENOL; ALKYL (C12-15) BENZOATE; FARNESOL; ISODECYL LAURATE; MAGNESIUM SULFATE, UNSPECIFIED FORM; NEOPENTYL GLYCOL DIETHYLHEXANOATE; PHENOXYETHANOL; POLYGLYCERYL-6 POLYRICINOLEATE; POTASSIUM SORBATE; PROPANEDIOL DICAPRYLATE; TOCOPHEROL; .ALPHA.-TOCOPHEROL ACETATE; TRIETHOXYCAPRYLYLSILANE

GM Collin®
SPF 25 UVA - UVB Urban Protection Veil

Product Facts / Drug Facts

ACTIVE INGREDIENT

Active ingredients: | Purpose
Zinc Oxide 13.3% | Sunscreen
Titanium Dioxide 3.8% | Sunscreen

Uses

- helps prevent sunburn.
- if used as directed with other sun protection measures (see Directions), decreases the risk of skin cancer and early skin aging caused by the sun.

Warnings

For external use only. Shake well before each use.

Do not useon damaged or broken skin.

WHEN USING

When using this productkeep out of eyes. Rinse with water to remove.

Stop use and ask a doctorif rash occurs.

Keep out of reach of children.

If swallowed, get medical help or contact a Poison Control Center right away.

Directions

Adults over 18 years old:

- apply liberally 15 minutes before sun exposure.
- reapply at least every 2 hours
- use a water-resistant sunscreen if swimming or sweating
- Sun Protection Measures: Spending time in the sun increases your risk of skin cancer and early skin aging.
  To decrease risk, regularly use a sunscreen with a Broad Spectrum SPF value of 15 or higher and other sun protection measures including:
  - limit time in the sun, especially from 10 a.m. – 2 p.m.
  - wear long-sleeved shirts, pants, hats and sunglasses.

Other information

- protect this product from excessive heat and direct sun.
- keep at room temperature (15 - 30°C / 59 - 86°F)

Inactive ingredients

1,2-HEXANEDIOL, ALUMINA, AQUA/WATER/EAU, ARGANIA SPINOSA KERNEL OIL, ASCORBYL PALMITATE, BISABOLOL, C12-15 ALKYL BENZOATE, FARNESOL, FRAGRANCE/PARFUM, HYDROGEN DIMETHICONE, ISODECYL LAURATE, MAGNESIUM SULFATE, NEOPENTYL GLYCOL DIETHYLHEXANOATE, PHENOXYETHANOL, POLYGLYCERYL-6 POLYHYDROXYSTEARATE, POLYGLYCERYL-6 POLYRICINOLEATE, POLYHYDROXYSTEARIC ACID, POTASSIUM SORBATE, PROPANEDIOL DICAPRYLATE, TOCOPHEROL, TOCOPHERYL ACETATE, TRIETHOXYCAPRYLYLSILANE.

Questions?

USA: 1 (800) 341-1531 / CANADA: 1 (800) 361-1263

DISTRIBUTED BY:
® LABORATOIRES DERMO-COSMETIK INC.
68 STINSON, MONTREAL, QUEBEC, CANADA H4N 2E7

PRINCIPAL DISPLAY PANEL - 100 ml Bottle Box

G.M. COLLIN®

C

SPF
25
UVA∙UVB

URBAN PROTECTION VEIL

Broad Spectrum
Mineral Sunscreen

NDC 64127-234-01
NPN 801xxxxx
06886

100 ml - 3.4 fl. oz.